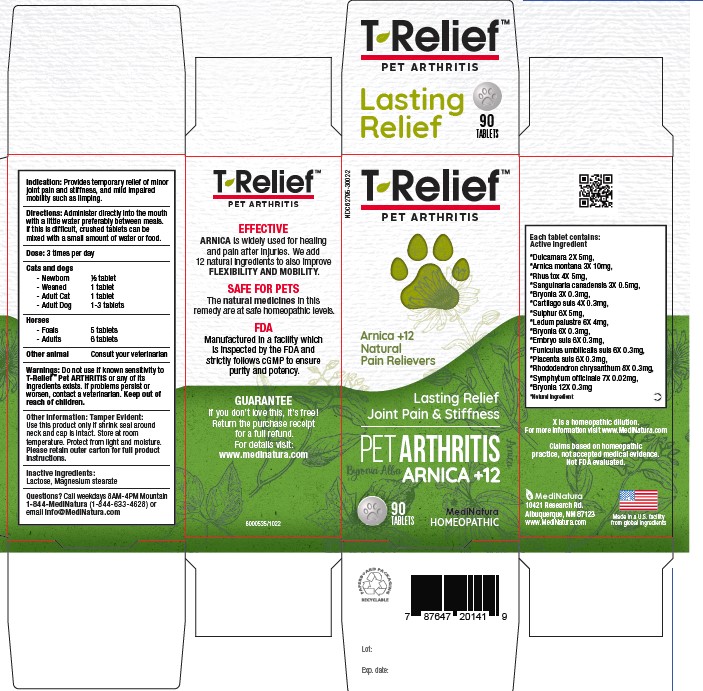 DRUG LABEL: T-Relief Pet Arthritis
NDC: 62795-3002 | Form: TABLET
Manufacturer: Medinatura New Mexico, Inc
Category: homeopathic | Type: OTC ANIMAL DRUG LABEL
Date: 20230927

ACTIVE INGREDIENTS: SOLANUM DULCAMARA TOP 2 [hp_X]/1 1; ARNICA MONTANA 3 [hp_X]/1 1; TOXICODENDRON PUBESCENS LEAF 4 [hp_X]/1 1; SANGUINARIA CANADENSIS ROOT 3 [hp_X]/1 1; BRYONIA ALBA ROOT 3 [hp_X]/1 1; SUS SCROFA CARTILAGE 4 [hp_X]/1 1; SULFUR 6 [hp_X]/1 1; LEDUM PALUSTRE TWIG 6 [hp_X]/1 1; SUS SCROFA UMBILICAL CORD 6 [hp_X]/1 1; SUS SCROFA PLACENTA 6 [hp_X]/1 1; RHODODENDRON AUREUM LEAF 8 [hp_X]/1 1; COMFREY ROOT 7 [hp_X]/1 1
INACTIVE INGREDIENTS: LACTOSE MONOHYDRATE; MAGNESIUM STEARATE

T-Relief Pet Arthritis

WARNINGS

Do not use if known sensitivity to T-Relief Pet Arthritis or any of its ingredients exists.
If problems persist or worsen, contact a veterinarian.

KEEP OUT OF REACH OF CHILDREN SECTION

Active Ingredients:

Each tablet contains: *Dulcamara 2X, 5 mg. *Arnica montana 3X, 10 mg. *Rhus toxicodendron 4X, 5 mg. *Sanguinaria canadensis 3X, 0.5 mg. *Bryonia alba 3x, 0.3 mg. *Cartiago suis, 4X 0.3 mg. *Sulfur 6X, 5 mg. *Ledum palustre 6X, 4 mg. *Bryonia alba 6X, 0.3 mg. *Embryo suis 6X, 0.3 mg. *Funiculus umbillicalis suis 6X, 0.3 mg. *Placenta totalis suis 6X, 0.3 mg. *Rhododendron chrysanthum 8X, 0.3 mg. *Symphytum officinale 7X.0.02 mg. *Bryonia alba 12X 0.3 mg.
*Natural Ingredients

Indications

Provides temporary relief of minor joint pain and stiffness, and mild impaired mobility such as limping

INACTIVE INGREDIENTS

Lactose, Magnesium Stearate

USES

Provides temporary relief of minor joint pain and stiffness, and mild impaired mobility such as limping.

DIRECTIONS

Administer directly into the mouth with a little water preferably between meals. If this is difficult, crushed tablets can be mixed with small amount of water or food.

PACKAGE LABEL

Add image transcription here...